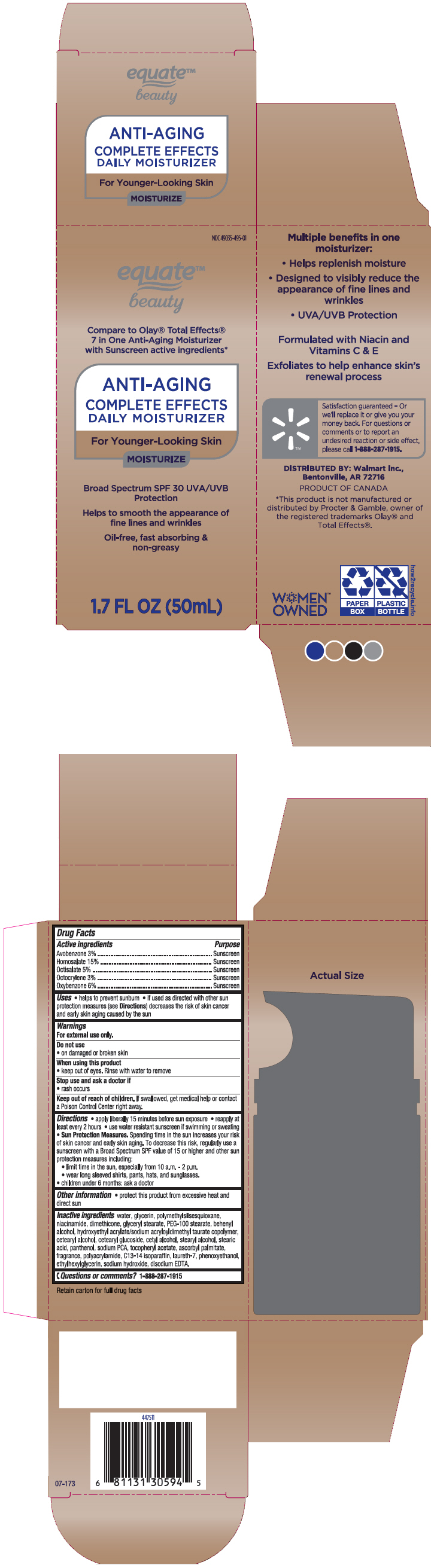 DRUG LABEL: Equate Beauty Daily Moisturizer SPF-30
NDC: 49035-495 | Form: LOTION
Manufacturer: Wal-Mart Stores, Inc.
Category: otc | Type: HUMAN OTC DRUG LABEL
Date: 20250110

ACTIVE INGREDIENTS: Avobenzone 30 mg/1 mL; Homosalate 150 mg/1 mL; Octisalate 50 mg/1 mL; Octocrylene 30 mg/1 mL; Oxybenzone 60 mg/1 mL
INACTIVE INGREDIENTS: Water; Glycerin; Polymethylsilsesquioxane (4.5 Microns); Niacinamide; Dimethicone; Glyceryl Monostearate; PEG-100 Stearate; Docosanol; HYDROXYETHYL ACRYLATE/SODIUM ACRYLOYLDIMETHYL TAURATE COPOLYMER (100000 MPA.S AT 1.5%); Cetostearyl Alcohol; Cetearyl Glucoside; Cetyl Alcohol; Stearyl Alcohol; Stearic Acid; Panthenol; Sodium Pyrrolidone Carboxylate; .ALPHA.-TOCOPHEROL ACETATE, DL-; Ascorbyl Palmitate; POLYACRYLAMIDE (1500 MW); C13-14 Isoparaffin; Laureth-7; Phenoxyethanol; Ethylhexylglycerin; Sodium Hydroxide; EDETATE DISODIUM

Equate™ Beauty Daily Moisturizer SPF-30
Sunscreen

Drug Facts

ACTIVE INGREDIENT

Active ingredients | Purpose
Avobenzone 3% | Sunscreen
Homosalate 15% | Sunscreen
Octisalate 5% | Sunscreen
Octocrylene 3% | Sunscreen
Oxybenzone 6% | Sunscreen

Uses

- helps to prevent sunburn
- if used as directed with other sun protection measures (see Directions) decreases the risk of skin cancer and early skin aging caused by the sun

Warnings

For external use only

Do not use

- on damaged or broken skin

When using this product

- keep out of eyes. Rinse with water to remove

Stop use and ask a doctor if

- rash occurs

Keep out of reach of children. If swallowed, get medical help or contact a Poison Control Center right away

Directions

- apply liberally 15 minutes before sun exposure
- reapply at least every 2 hours
- use water resistant sunscreen if swimming or sweating
- Sun Protection Measures. Spending time in the sun increases your risk of skin cancer and early skin aging. To decrease this risk, regularly use a sunscreen with a Broad Spectrum SPF value of 15 or higher and other sun protection measures including:
  - limit time in the sun, especially from 10 a.m. – 2 p.m.
  - wear long sleeve sleeved shirts, pants, hats, and sunglasses.
- children under 6 months: ask a doctor

Other information

- protect this product from excessive heat and direct sun

Inactive ingredients

water, glycerin, polymethylsilsesquioxane, niacinamide, dimethicone, glyceryl stearate, PEG-100 stearate, behenyl alcohol, hydroxyethyl acrylate/sodium acryloyldimethyl taurate copolymer, cetearyl alcohol, cetearyl glucoside, cetyl alcohol, stearyl alcohol, stearic acid, panthenol, sodium PCA, tocopheryl acetate, ascorbyl palmitate, fragrance, polyacrylamide, C13-14 Isoparaffin, laureth-7, phenoxyethanol, ethylhexylglycerin, sodium hydroxide, disodium EDTA.

Questions or comments?

1-888-287-1915

DISTRIBUTED BY: Walmart Inc.,
Bentonville, AR 72716

PRINCIPAL DISPLAY PANEL - 50 mL Cylinder Carton

NDC 49035-495-01

equate™
beauty

Compare to Olay® Total Effects®
7 in One Anti-Aging Moisturizer
with Sunscreen active ingredients*

ANTI-AGING

COMPLETE EFFECTS
DAILY MOISTURIZER

For Younger-Looking Skin

MOISTURIZE

Broad Spectrum SPF 30 UVA/UVB
Protection

Helps to smooth the appearance of
fine lines and wrinkles

Oil-free, fast absorbing &
non-greasy

1.7 FL OZ (50mL)